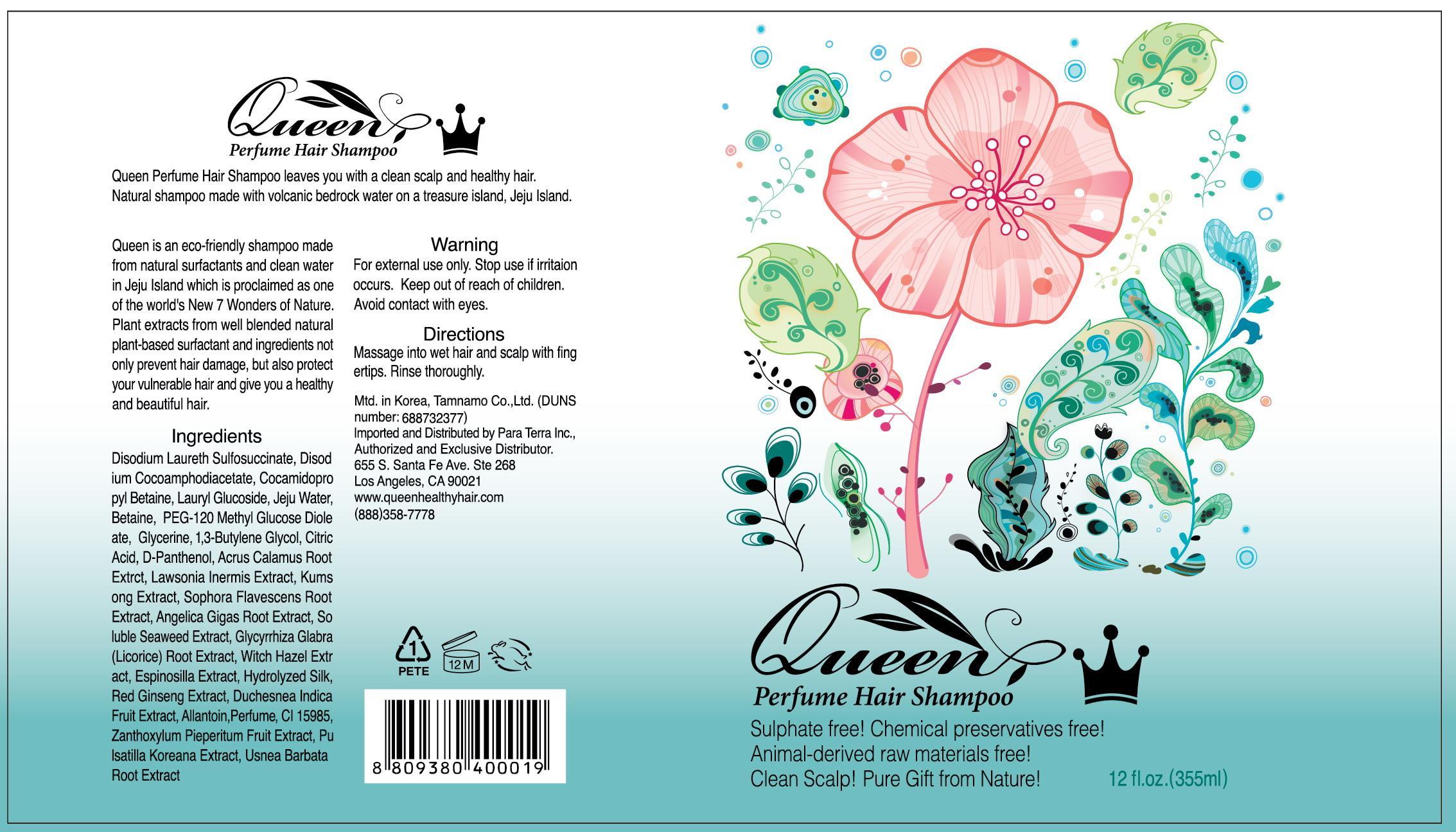 DRUG LABEL: Queen Perfume Hair
NDC: 60344-5001 | Form: SHAMPOO
Manufacturer: Tamnamo Co., Ltd
Category: otc | Type: HUMAN OTC DRUG LABEL
Date: 20140130

ACTIVE INGREDIENTS: GLYCERIN 0.02 mg/1 mL
INACTIVE INGREDIENTS: BETAINE; COCAMIDOPROPYL BETAINE; LAURYL GLUCOSIDE; CITRIC ACID MONOHYDRATE; DEXPANTHENOL; ALLANTOIN

Drug Facts

ACTIVE INGREDIENT

glycerin

INACTIVE INGREDIENT

Disodium Laureth Sulfosuccinate, Disodium Cocoamphodiacetate, Cocamidopropyl Betaine, Lauryl Glucoside, Jeju Water, Betaine, PEG-120 Methyl Glucose Dioleate, 1,3-Butylene Glycol, Citric Acid, D-Panthenol, Acrus Calamus Root Extrct, Lawsonia Inermis Extract, Kumsong Extract, Sophora Flavescens Root Extract, Angelica Gigas Root Extract, Soluble Seaweed Extract, Glycyrrhiza Glabra (Licorice)Root Extract, Witch Hazel Extract, Espinosilla Extract, Hydrolyzed Silk, Red Ginseng Extract, Duchesnea Indica Fruit Extract, Allantoin, Perfume, CI 15985, Zanthoxylum Pieperitum Fruit Extract, Pulsatilla Koreana Extract, Usnea Barbata Root Extract

PURPOSE

supplying moisture and nutrient to scalp and hair

keep out of reach of the children

INDICATIONS AND USAGE

massage into wet hair and scalp with fingertips
rinse thoroughly

stop use if irritation occurs
avoid contact with eyes

DOSAGE AND ADMINISTRATION

for external use only